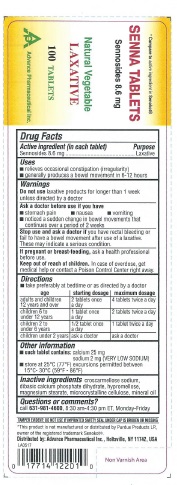 DRUG LABEL: Senna
NDC: 17714-122 | Form: TABLET
Manufacturer: Advance Pharmaceutical Inc.
Category: otc | Type: HUMAN OTC DRUG LABEL
Date: 20171030

ACTIVE INGREDIENTS: SENNOSIDES A AND B 8.6 mg/1 1
INACTIVE INGREDIENTS: CROSCARMELLOSE SODIUM; CALCIUM PHOSPHATE, DIBASIC, DIHYDRATE; HYPROMELLOSES; MAGNESIUM STEARATE; CELLULOSE, MICROCRYSTALLINE; MINERAL OIL

Senna 8.6mg tabs

Active ingredient (in each tablet)

Sennosides 8.6 mg

Purpose

Laxative

Uses

- relieves occasional constipation (irregularity)
- generally produces a bowel movement in 6 - 12 hours

Warnings

Do not use

- laxative products for longer than 1 week unless directed by a doctor

Ask a doctor before use if you have

- stomach pain
- nausea
- vomiting
- noticed a sudden change in bowel habits that continues over a period of 2 weeks

Stop use and ask a doctor if

you have rectal bleeding or fail to have a bowel movement after use of a laxative. These may indicate a serious condition.

If pregnant or breast-feeding,

ask a health professional before use.

Keep out of reach of children.

In case of overdose, get medical help or contact a Poison Control Center right away.

Directions

- take preferably at bedtime or as directed by a doctor

a ge | starting dosage | maximum dosage
adults and children 12 years of age or older | 2 tablets once a day | 4 tablets twice a day
children 6 to under 12 years | 1 tablet once a day | 2 tablets twice a day
children 2 to under 6 years | 1/2 tablet once a day | 1 tablet twice a day
children under 2 years | ask a doctor | ask a doctor

Other information

- each tablet contains: calcium 25 mg, sodium 2mg (very low sodium)
- store at 25ºC (77ºF); excursions permitted between 15º-30ºC (59º-86ºF)

Inactive ingredients

croscarmellose sodium, dibasic calcium phosphate dihydrate, hypromellose, , magnesium stearate, microcrystalline cellulose, mineral oil

Questions or comments?

call 631-981-4600, 8.30 am-4.30 pm ET, Monday - Friday
TAMPER EVIDENT: DO NOT USE IF IMPRINTED SAFETY SEAL UNDER CAP IS BROKEN OR MISSING

Principal Display Panel

NDC: 17714-122-01

Senna 8.6mg